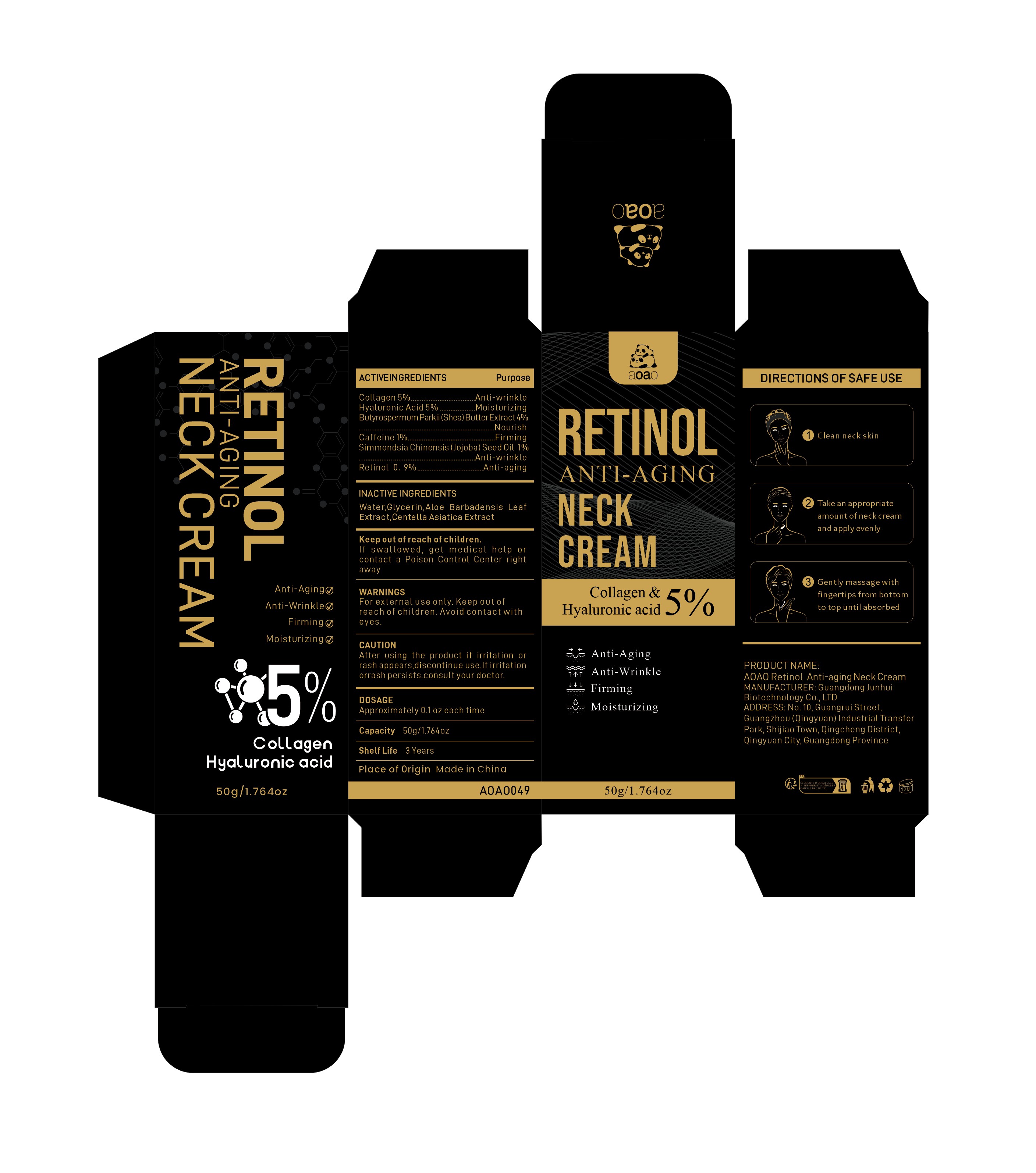 DRUG LABEL: AOAO Retinol Anti-aging Neck Cream
NDC: 84509-046 | Form: CREAM
Manufacturer: Guangdong Junhui Biotechnology Co., LTD
Category: otc | Type: HUMAN OTC DRUG LABEL
Date: 20241107

ACTIVE INGREDIENTS: SIMMONDSIA CHINENSIS (JOJOBA) SEED OIL 500 mg/50 g; RETINOL 450 mg/50 g; COLLAGEN, SOLUBLE, FISH SKIN 2500 mg/50 g; CAFFEINE 500 mg/50 g; BUTYROSPERMUM PARKII (SHEA) BUTTER EXTRACT 2000 mg/50 g; HYALURONIC ACID 2500 mg/50 g
INACTIVE INGREDIENTS: WATER; ALOE BARBADENSIS LEAF EXTRACT; CENTELLA ASIATICA TRITERPENOIDS; GLYCERIN

Active Ingredients

Collagen 5%
Butyrospermum Parkii (Shea) Butter Extract 4%
Hyaluronic Acid 5%
Caffeine 1%
Simmondsia Chinensis (Jojoba) Seed Oil 1%
Retinol 0.9%

Purpose

Anti-wrinkle
Nourish
Moisturizing
Firming
Anti-aging

Uses

1、Clean neck skin
2、Take an appropriateamount of neck creamand apply evenly
3、Gently massagewith fingertipsfrom bottom to topuntil absorbed

Warnings

For external use only. Keep out ofreach of children.Avoid contact with eyes

Keep out of reach of children

If swallowed, get medical help or contact a Poison Control Center right away

CAUTION

After using the product if irritation or rash appears,discontinue use.If irritation or
rash persists.consult your doctor.

Inactive Ingredients

Water,Glycerin，Aloe Barbadensis Leaf Extract，Centella Asiatica Extract

DOSAGE

Approximately 0.1oz each time

Product Name

AOAO Retinol Anti-aging Neck Cream

Manufacturer

Guangdong Junhui Biotechnology Co., LTD

Address

No. 10, Guangrui Street, Guangzhou (Qingyuan) Industrial Transfer Park, Shijiao Town, Qingcheng District, Qingyuan City, Guangdong Province

Capacity

50g/1.764oz

Shelf Life

3 Years

Place of Origin

Made in China